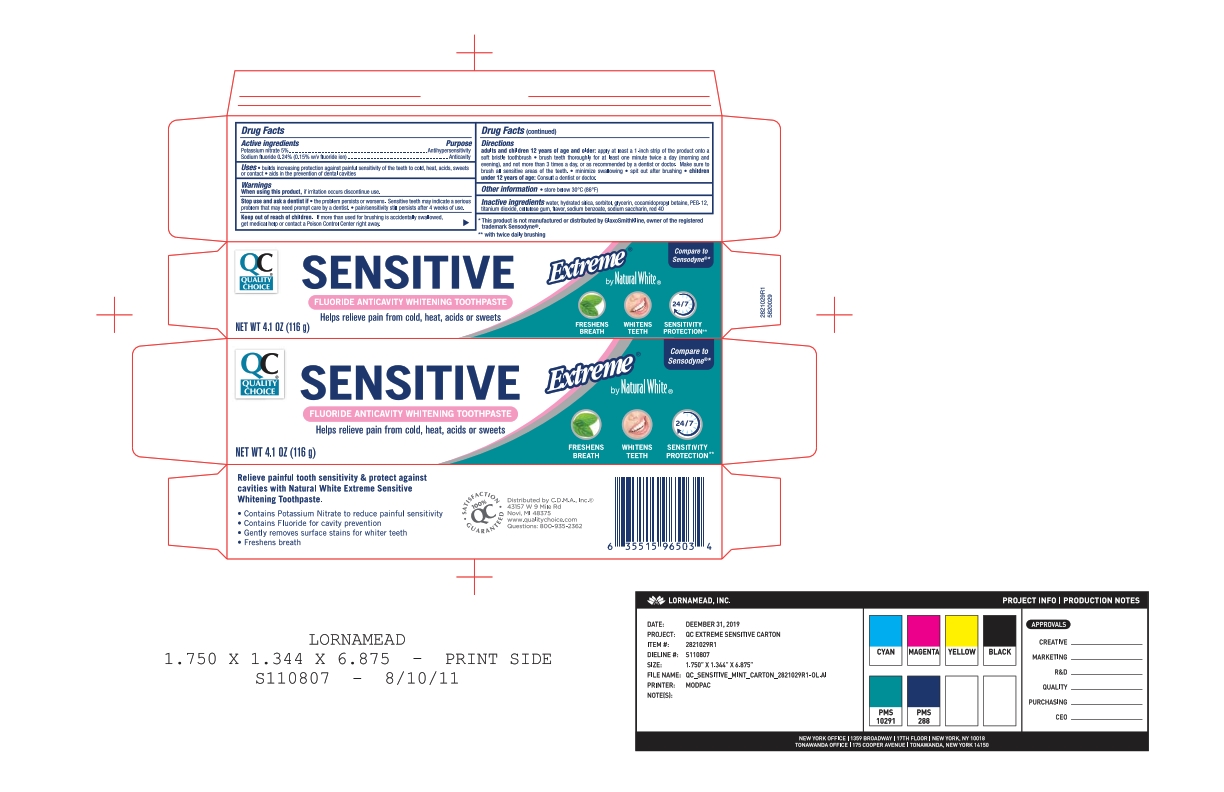 DRUG LABEL: Quality Choice
NDC: 63868-172 | Form: PASTE, DENTIFRICE
Manufacturer: CHAIN DRUG MARKETING ASSOCIATION INC
Category: otc | Type: HUMAN OTC DRUG LABEL
Date: 20251112

ACTIVE INGREDIENTS: SODIUM FLUORIDE 0.15 g/100 g; POTASSIUM NITRATE 5 g/100 g
INACTIVE INGREDIENTS: SACCHARIN SODIUM; SODIUM TRIPOLYPHOSPHATE; WATER; POLYETHYLENE GLYCOL 400; SORBITOL; TITANIUM DIOXIDE; SODIUM HYDROXIDE; GLYCERIN; XANTHAN GUM; HYDRATED SILICA; COCAMIDOPROPYL BETAINE; SODIUM METHYL COCOYL TAURATE

5820029 QC Nat White Ex Sens

Active ingredients / Purpose

Potassium nitrate 5%....................................................Antihypersensitivity

Sodium fluoride 0.24% (0.15% w/v fluoride ion)............Anticavity

Uses

- builds increasing protection against painful sensitivity of the teeth to cold, heat, acids, sweets or contact
- aids in the prevention of dental cavities

When using this product do not use longer than 4 weeks unless recommended by a dentist or physician. See your dentist if the problem worsens. Sensitive teeth may indicate a serious problem that may need prompt care by a dentist.

Keep out of reach of children. If more than used for brushing is accidentally swallowed, get medical help or contact a Poison Control Center right away.

Directions

Brush teeth thoroughly for at least one minute, preferably after each meal or at least twice a day (morning and evening) or as recommended by a dentist or physican. Make sure to brush all sensitive areas of the teeth.

DOSAGE AND ADMINISTRATION

Apply at least a 1-inch strip of the product onto a soft bristle toothbrush. Children under 12 years of age: consult a dentist or a doctor.

Other Information

Store in a cool dry place. Keep tube capped when not in use.

Inactive ingredients

cocamidopropyl betaine, flavor, glycerin, hydrated silica, PEG-8, sodium hydroxide, sodium methyl cocoyl taurate, sodium saccharin, sodium tripolyphosphate, sorbitol, titanium dioxide, water, xanthan gum